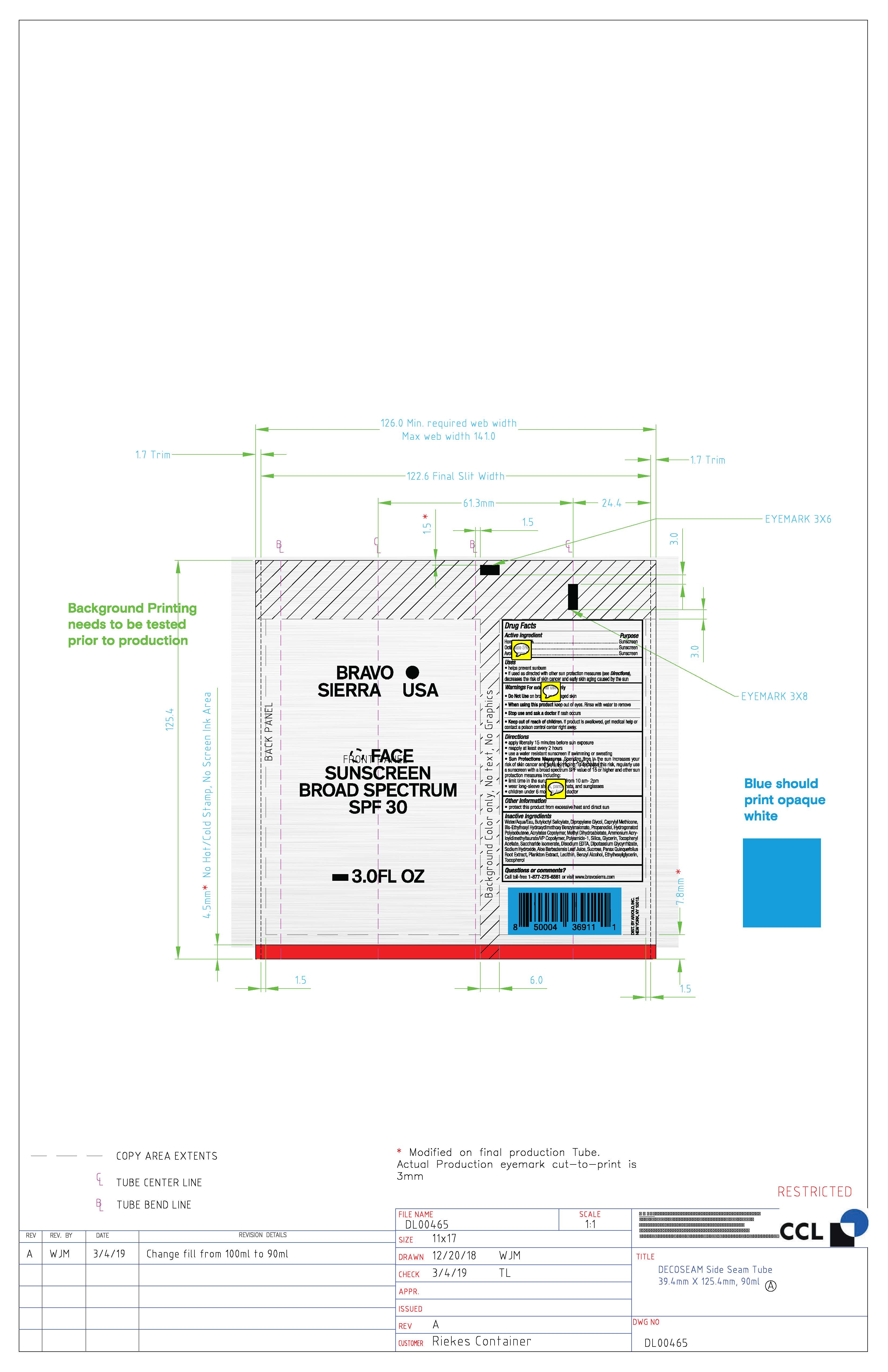 DRUG LABEL: Bravo Sierra USA Face Sunscreen Broad Spectrum SPF 30
NDC: 73206-010 | Form: LOTION
Manufacturer: ARJOLO, INC.
Category: otc | Type: HUMAN OTC DRUG LABEL
Date: 20190706

ACTIVE INGREDIENTS: AVOBENZONE 3 g/100 g; HOMOSALATE 10 g/100 g; OCTISALATE 5 g/100 g
INACTIVE INGREDIENTS: WATER; BUTYLOCTYL SALICYLATE; DIPROPYLENE GLYCOL; CAPRYLYL CAPRYLATE; BIS-ETHYLHEXYL HYDROXYDIMETHOXY BENZYLMALONATE; PROPANEDIOL; HYDROGENATED POLYBUTENE (1300 MW); METHYL DIHYDROABIETATE; AMMONIUM ACRYLOYLDIMETHYLTAURATE/VP COPOLYMER; POLYAMIDE-3 (12000 MW); SILICON; GLYCERIN; .ALPHA.-TOCOPHEROL ACETATE; SACCHARIDE ISOMERATE; DISODIUM EDTA-COPPER; SODIUM HYDROXIDE; ALOE VERA LEAF; SUCROSE; PANAX QUINQUEFOLIUS WHOLE; LECITHIN, SUNFLOWER; BENZYL ALCOHOL; ETHYLHEXYLGLYCERIN; TOCOPHEROL

DRUG FACTS

Active Ingredients

Avobenzone 3%

Homosalate 10%

Octisalate 5%

Uses

• helps prevent sunburn • if used as directed with other
sun protection measures (see Directions), decreases the
risk of skin cancer and early skin aging caused by the sun

Warnings

For external use only
Do not use on damaged or broken skin
When using this product keep out of eyes. Rinse with water to remove.
Stop use and ask a docor if rash occurs
Keep out of reach of children. If swalled, get medical help or contact a Poison Control Center right away.

Directions

• apply generously 15 minutes before sun exposure
• reapply at least every 2 hours
• use a water-resistant sunscreen if swimming or sweating
• Sun Protection Measures. Spending time in the sun
increases your risk of skin cancer and early skin aging. To decrease
this risk, regularly use a sunscreen with a Broad Spectrum SPF
value of 15 or higher and other sun protection measures including:
• limit time in the sun, especially from 10 a.m. - 2 p.m.
• wear long-sleeved shirts, pants, hats, and sunglasses
• children under 6 months of age: Ask a doctor

Inactive ingredients

Water/Aqua/Eau, Butyloctyl Salicylate, Dipropylene Glycol, Caprylyl Methicone, Bis-Ethylhexyl Hydroxydimethoxy Benzylmalonate, Propanediol, Hydrogenated Polyisobutene, Acrylates Copolymer, Methyl Dihydroabietate, Ammonium Acry loyldimethyltaurate/P Copolymer, Polyamide-1, Silica, Glycerin, Tocopheryl Acetate, Saccharide Isomerate, Disodium EDTA, Dipotassium Glycyrrhizate, Sodium Hydroxide, Aloe Barbadensis Leaf Juice, Sucrose, Panax Quinquefolius Root Extract, Plankton Extract, Lecithin, Benzyl Alcohol, Ethylhexylglycerin, Tocopherol

Other Information

• protect the product in this container from excessive heat and direct sun

Questions or Comments?

Call toll-free 1-877-275-6561 or visit www.bravosierra.com